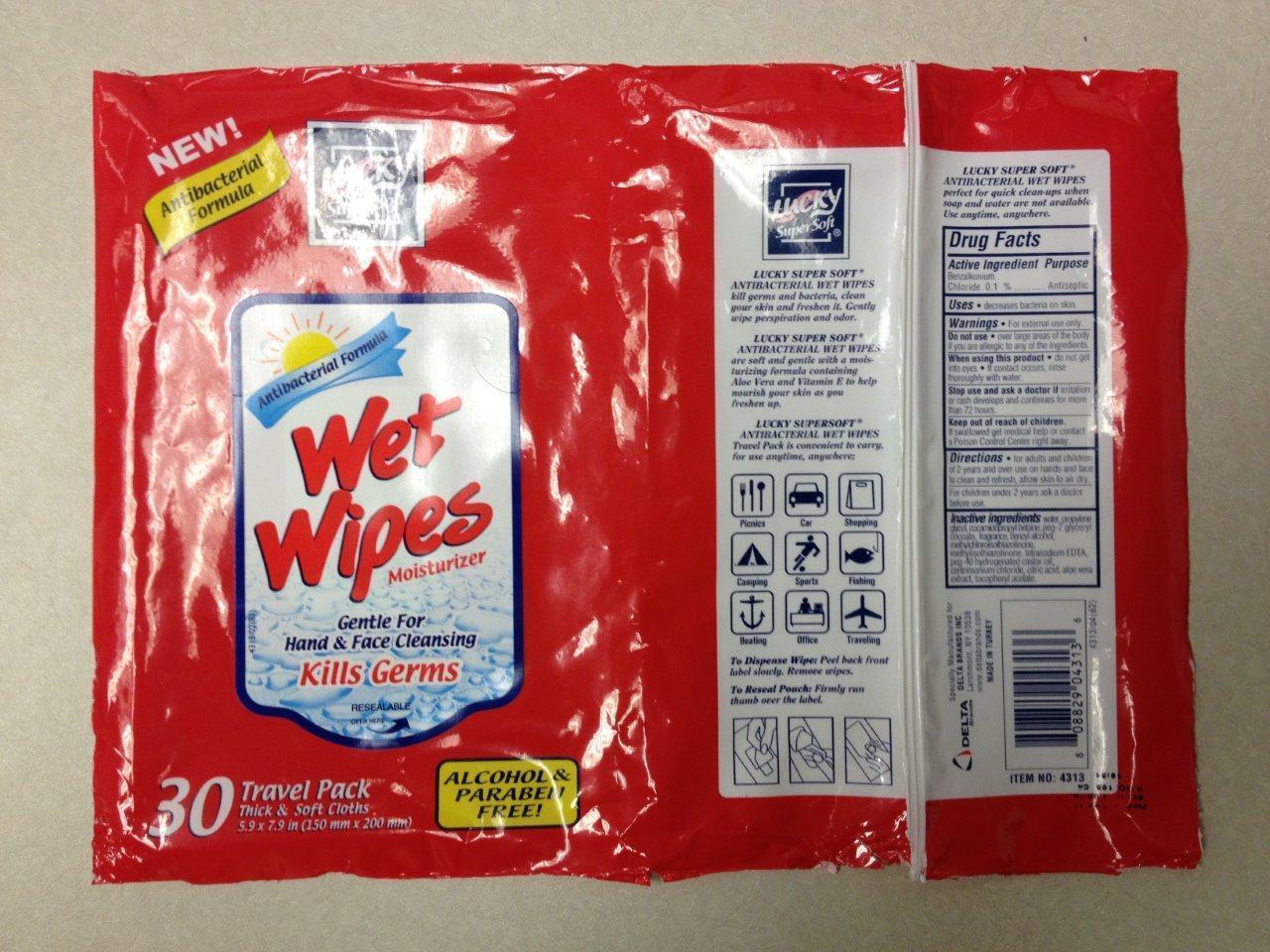 DRUG LABEL: Wet Wipes
NDC: 70140-001 | Form: SWAB
Manufacturer: GULSAH URETIM PAZARLAMA - HUSEY IN KAYA
Category: otc | Type: HUMAN OTC DRUG LABEL
Date: 20171010

ACTIVE INGREDIENTS: BENZALKONIUM CHLORIDE 0.1 g/1 1
INACTIVE INGREDIENTS: WATER; PROPYLENE GLYCOL; COCAMIDOPROPYL BETAINE; BENZYL ALCOHOL; METHYLCHLOROISOTHIAZOLINONE; METHYLISOTHIAZOLINONE; EDETATE SODIUM; CETRIMONIUM CHLORIDE; CITRIC ACID MONOHYDRATE; ALOE VERA LEAF; ALPHA-TOCOPHEROL ACETATE

Drug Facts

Active Ingredient

Benzalkonium Chloride 0.1%

Purpose

Antiseptic

Uses

•decreases bacteria on the skin

Warnings

•For external use only

Do not use

•Over large areas of the body if you are allergic to any of the ingredients

When using this product

•do not get into eyes. •If contact occurs, rinse thoroughly with water.

Stop use

Stop use and ask a doctor if irritation or rash develops and continues for more than 72 hours

Keep out of reach of children. If swallowed get medical help or contact a Poison Control Center right away.

Directions

• for adults and children 2 years and over use on hands and face to clean and refresh, allow skin to air dry. For children under 2 years of age ask a doctor before use.

Inactive Ingredients

water, propylene glycol, cocamidopropyl betaine, peg-7 glyceryl cocoate, fragrance, benzyl alcohol, methylchloroisothiazolinine, methylisothiazolinone, tetrasodium EDTA, peg-40 hydrogenated castor oil, cetrimonium chloride, citric acid, aloe vera extract, alphatocopherol acetate